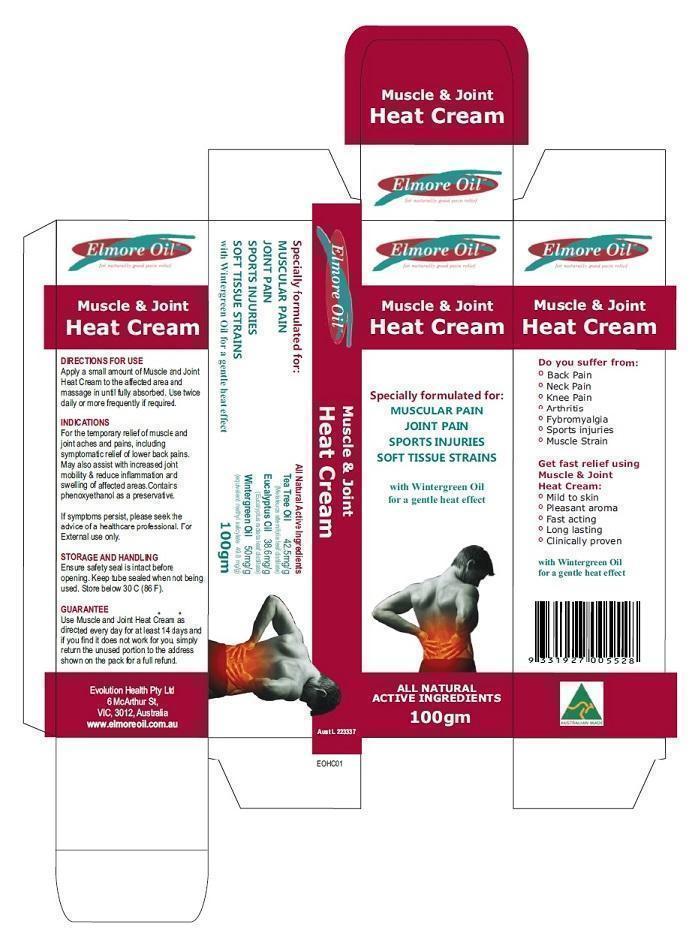 DRUG LABEL: Muscle and Joint Heat Cream
NDC: 69594-003 | Form: CREAM
Manufacturer: Ultra Mix (Aust) Pty Ltd 
Category: otc | Type: HUMAN OTC DRUG LABEL
Date: 20160408

ACTIVE INGREDIENTS: EUCALYPTUS OIL 38.6 mg/1 g; TEA TREE OIL 42.5 mg/1 g; METHYL SALICYLATE 50 mg/1 g
INACTIVE INGREDIENTS: PHENOXYETHANOL

Muscle and Joint Heat Cream

Actives

Tea Tree Oil (Melaleuca Alternifolia) - 42.5 mg/g
Eucalyptus Oil (Eucalyptus radiata) - 38.6 mg/g

Winter Green Oil (Methyl Salicylate)- 50 mg/g

Purpose

Pain relief cream to assist with relief of joint and muscle pain

Indication and Usage

For the temporary relief of muscle andjoint aches and pains, includingsymptomatic relief of lower back pains.

May also assist with increased jointmobility & reduce inflammation andswelling of affected areas.

Contains phenoxyethanol as a preservative.

Dosage and Administration

Apply a small amount of Muscle and Joint Heat Cream to the affected area and massage in until fully absorbed. Use twice

daily or more frequently if required.

Warnings

For external use only.

Ensure safety seal is intact beforeopening. Keep tube sealed when not being used. Store below 30^0 C (86 F).

Keep out of reach from Children